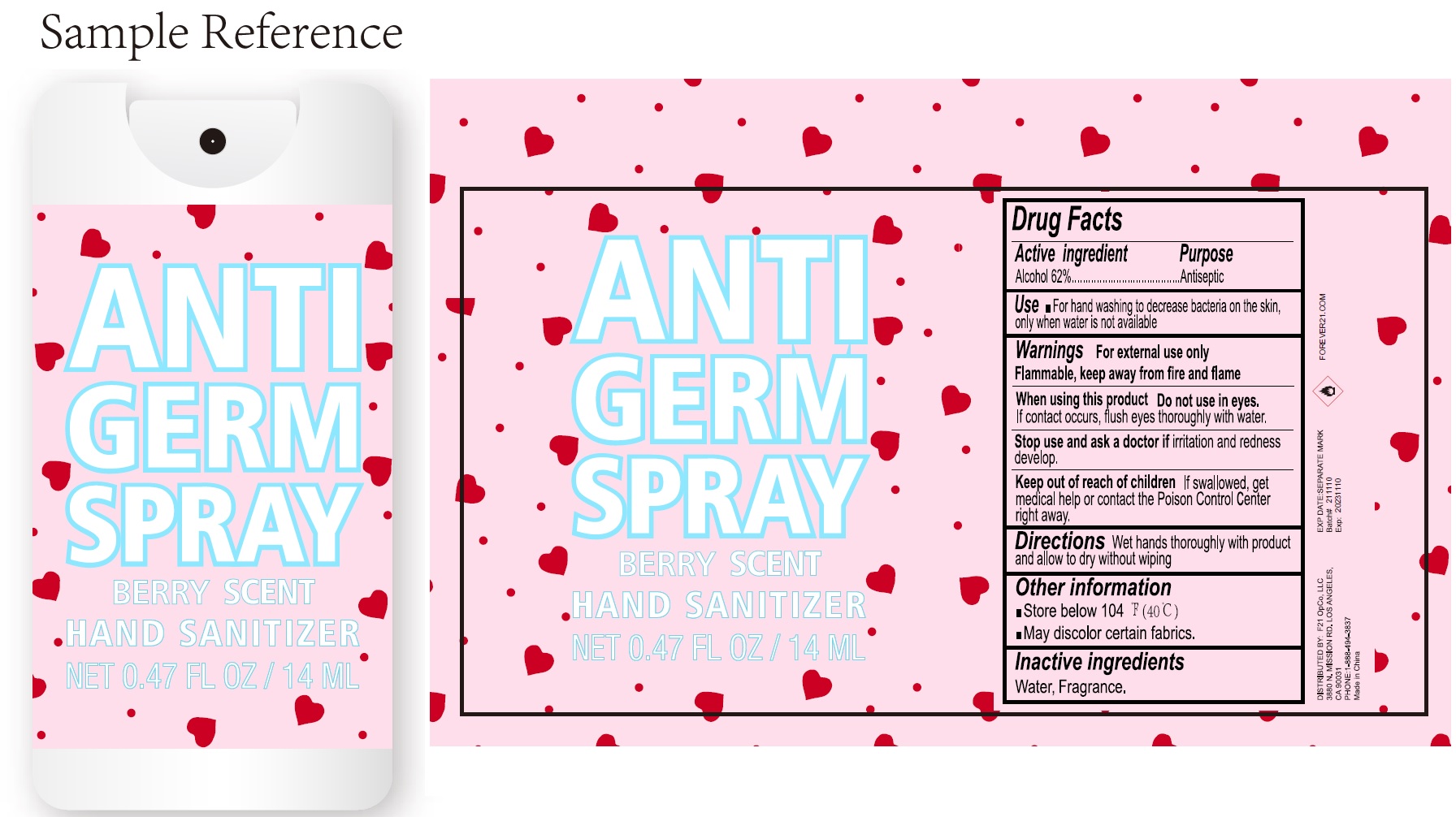 DRUG LABEL: BERRY SCENT ANTI GERM
NDC: 81670-003 | Form: SPRAY
Manufacturer: F21 OpCo,LLC
Category: otc | Type: HUMAN OTC DRUG LABEL
Date: 20231026

ACTIVE INGREDIENTS: ALCOHOL 62 mL/100 mL
INACTIVE INGREDIENTS: WATER

BERRY SCENT ANTI GERM SPRAY

Active ingredient

Alcohol 62%

Purpose

Antiseptic

Use

- For hand washing to decrease bacteria on the skin, only when water is not available

Warnings

For external use only

Flammable, keep away from fire and flame

When using this product

If contact occurs, flush eyes thoroughly with water. Do not use in eyes.

Stop use and ask a doctor if

irritation and redness develop.

Keep out of reach of children

If swallowed, get medical help or contact the Poison Control Center right away.

Directions

Wet hands thoroughly with product and allow to dry without wiping

Other information

- Store below 104 °F(40 °C)
- May discolor certain fabrics.

Inactive ingredients

Water, Fragrance.